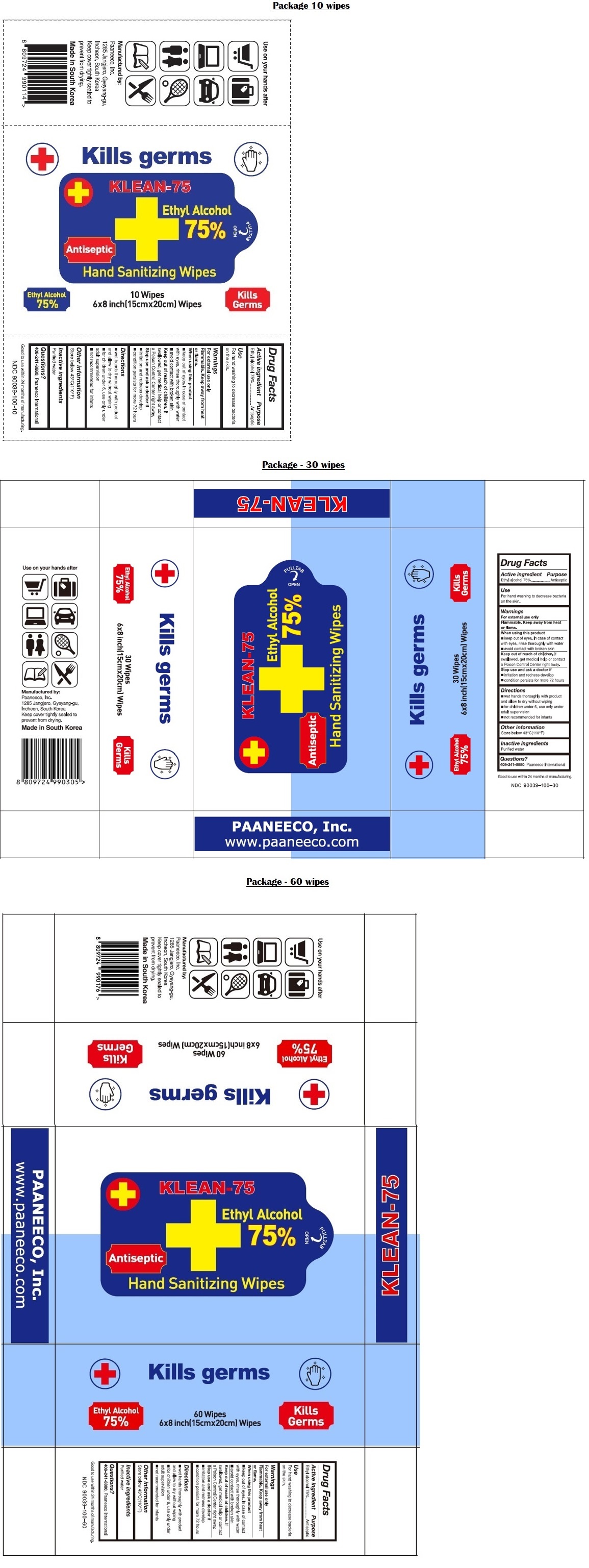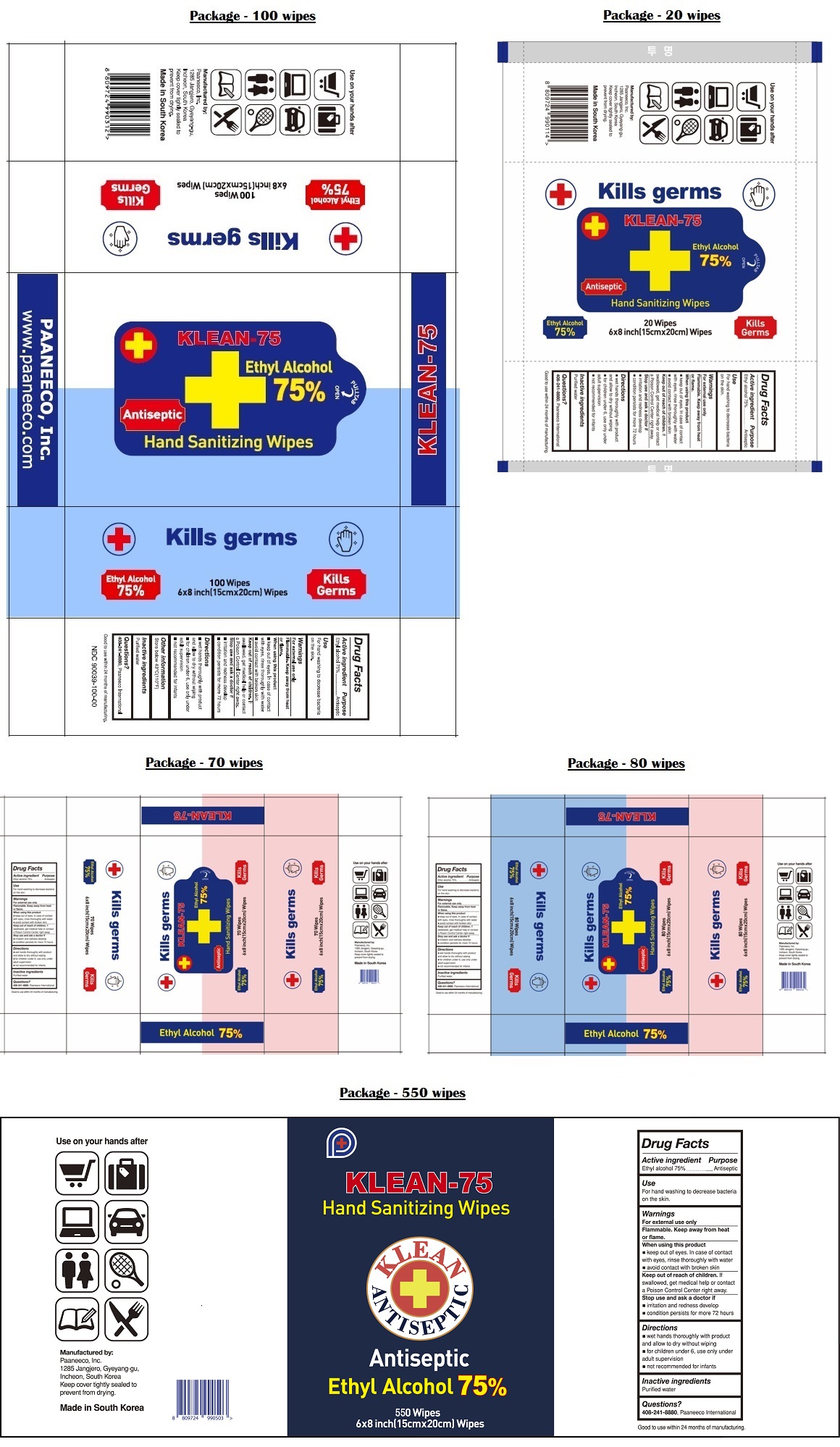 DRUG LABEL: KLEAN-75
NDC: 90039-100 | Form: CLOTH
Manufacturer: Paaneeco, Inc.
Category: otc | Type: HUMAN OTC DRUG LABEL
Date: 20211230

ACTIVE INGREDIENTS: ALCOHOL 75 mL/100 mL
INACTIVE INGREDIENTS: WATER

KLEAN-75 Hand Sanitizing Wipes

Active ingredient

Ethyl alcohol 75%

Purpose

Antiseptic

Use

For hand washing to decrease bacteria on the skin.

Warnings

For external use only

Flammable. Keep away from heat or flame.

When using this product

■ keep out of eyes. In case of contact with eyes, rinse thoroughly with water

■ avoid contact with broken skin

Stop use and ask a doctor if

■ irritation and redness develop

■ condition persists for more 72 hours

Keep out of reach of children. If swallowed, get medical help or contact a Poison Control Center right away.

Directions

■ wet hands thoroughly with product and allow to dry without wiping

■ for children under 6, use only under adult supervision

■ not recommended for infants

Other information

Store below 43°C(110°F)

Inactive ingredients

Purified water

Questions?

408-241-8880, Paaneeco International

Kills germs

Good to use within 24 months of manufacturing.

Use on your hands

Manufactured by:

Paaneeco, Inc.

1285, Jangjero, Gyeyang-gu,

Incheon, South Korea

Keep cover tightly sealed to prevent from drying.

Made in South Korea